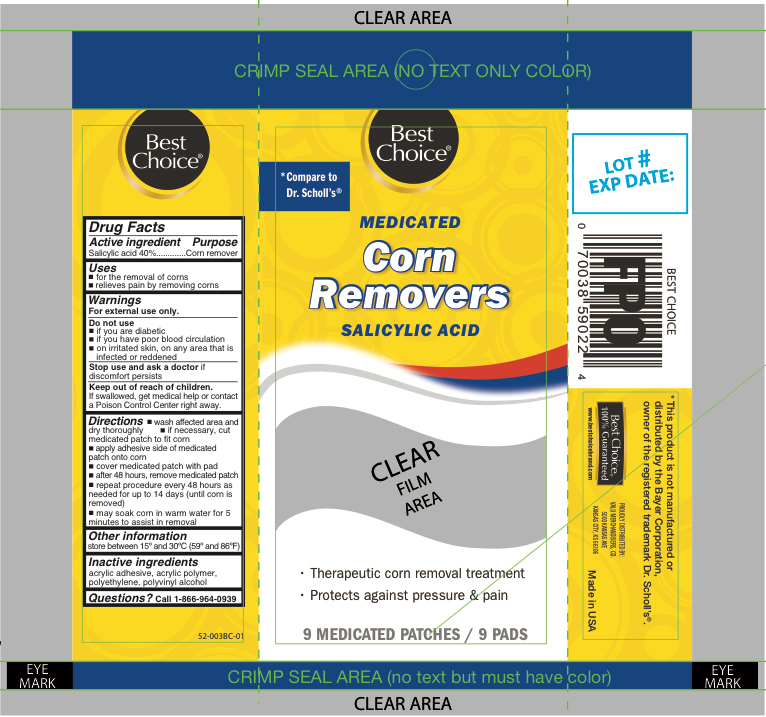 DRUG LABEL: Salicylic Acid
NDC: 63941-542 | Form: PATCH
Manufacturer: VALU MERCHANDISERS, CO
Category: otc | Type: HUMAN OTC DRUG LABEL
Date: 20260115

ACTIVE INGREDIENTS: SALICYLIC ACID 40 mg/9 1
INACTIVE INGREDIENTS: HIGH DENSITY POLYETHYLENE; POLYVINYL ALCOHOL

Best Choice Medicated Corn Removers

Active ingredient

Salicylic acid 40%

Purpose

Corn remover

Uses

- for the removal of corns
- relieves pain by removing corns

Warnings

For external use only.

Do not use

- if you are diabetic
- have poor blood circulation
- on irritated skin, or any area that is infected or reddened

Stop use and ask a doctor if discomfort persists

Keep out of reach of children.

If swallowed, get medical help or contact a Poison Control Center right away.

Directions

- wash affected area and dry area thoroughly
- if necessary, cut medicated patch to fit corn
- apply adhesive side down of medicated patch onto corn
- cover medicated patch with padafter 48 hours, remove medicated patch
- repeat procedure every 48 hours as needed for up to 14 days (until corn is removed)
- may soak corn in warm water for 5 minutes to assist in removal

Other information

store between 15°C to 30°C (59°F to 86°F)

Inactive ingredients

acrylic adhesive, acrylic polymer, polyethylene, polyvinyl alcohol

Questions?

call 1-866-964-0939

Principal Display Panel

Best Choice

Medicated

Corn Removers
Salicylic Acid

- Therapeautic corn removal treatment
- Protects against pressure & pain

9 Medicated Patches/ 9 Pads